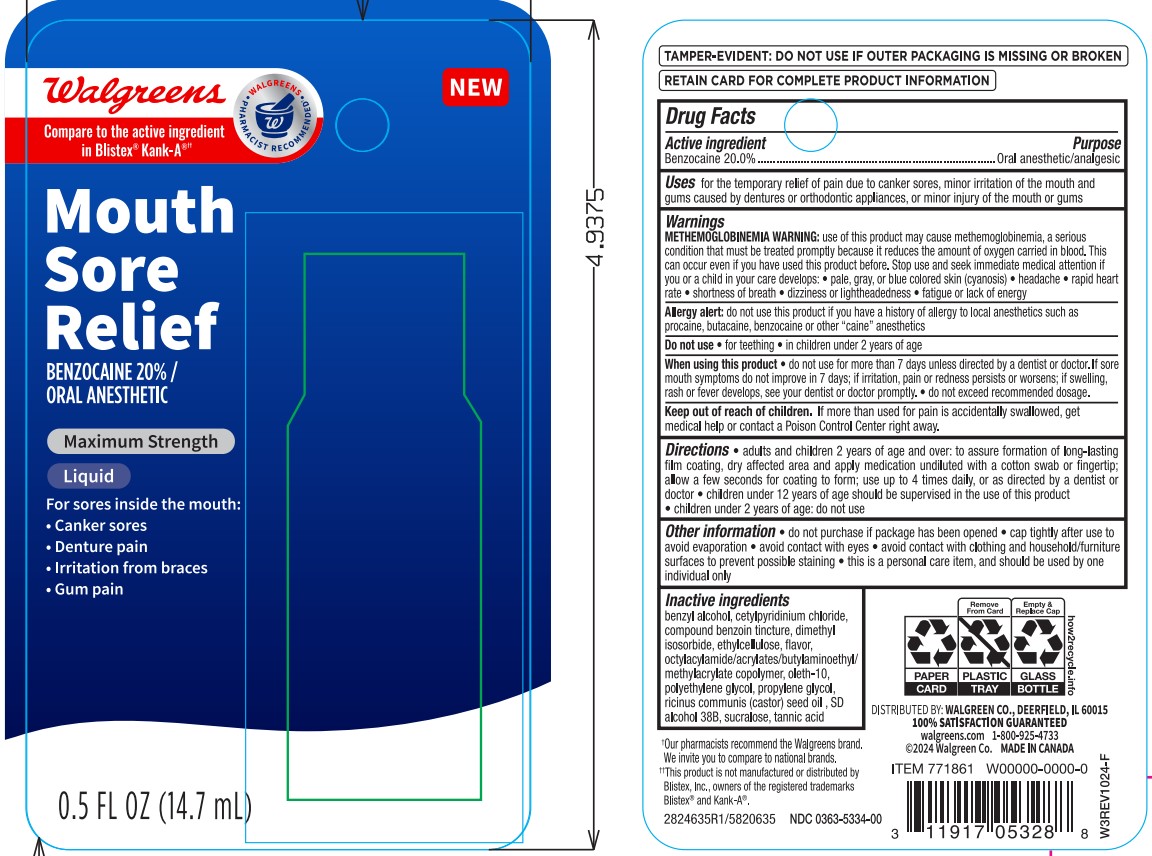 DRUG LABEL: Walgreens Mouth Sore Relief
NDC: 0363-5334 | Form: LIQUID
Manufacturer: Walgreens
Category: otc | Type: HUMAN OTC DRUG LABEL
Date: 20250812

ACTIVE INGREDIENTS: BENZOCAINE 200 mg/1 mL
INACTIVE INGREDIENTS: OLETH-10; DIMETHYL ISOSORBIDE; POLYETHYLENE GLYCOL 300; BENZOIN, (+/-)-; ACRYLATE/BUTYLAMINOETHYL METHACRYLATE/METHYL ACRYLATE/METHYL METHACRYLATE/OCTYLACRYLAMIDE COPOLYMER (40000 WAMW); CETYLPYRIDINIUM CHLORIDE; BENZYL ALCOHOL; PROPYLENE GLYCOL; SUCRALOSE; ETHYLCELLULOSE, UNSPECIFIED; ALCOHOL; RICINUS COMMUNIS SEED; TANNIC ACID

5820635 Walgreens Mouth Sore Relief (Kanka, 8015303)

ACTIVE INGREDIENT

Benzocaine 20%

PURPOSE

Oral anesthetic/analgesic

INDICATIONS AND USAGE

for the temporary relief of pain due to the canker sores, minor irritation of the mouth and gums caused by dentures or othodontic appliances, or minor injury of the mouth or gums

WARNINGS

Methemoglobinemia warning: use of this product may cuase methemoglobinemia, a serious condition that must be treated promptly because it reduces the amount of oygen carried in blood. This can occur even if you have used this product before. Stop use and seek immediate medical attention if you or a child in your care develops:

- plae, gray, or blue colored skin (cyanosis)
- headache
- rapid heart rate
- shortness of breath
- dizziness of lightheadedness
- fatigue or lack of energy

Allergy alert: do not use this product if you have a history of allergy to local anesthetics such as procaine, butacaine, benzocaine or other caine anesthetics

Keep out of reach of children. If more than used for pain is accidentally swallowed, get medical help or contact a Poison Control Center right away.

DOSAGE AND ADMINISTRATION

adults and children 2 years of age and over: to assure formation of long0lasting film coating, dry affected area and apply medication undiluted with a cotton swab or fingertip; allow a few seconds for coating to for; use up to 4 times daily, or as directed by a dentist or doctor

children under 12 years of age should be supervised in the use of this product

children under 2 years of age: do not use

INACTIVE INGREDIENT

benzyl alcohol, cetylpyridinium chloride, compound benzoin tincture, dimethyl isosorbide, ethylcellulose, flavor, octylacylamide/acrylates/butylaminoethyl/methylacrylate copolymer, oleth-10, polyethylene glycol, propylene glycol, ricinus communis (castor) seed oil , SD alcohol 38B, sucralose, tannic acid